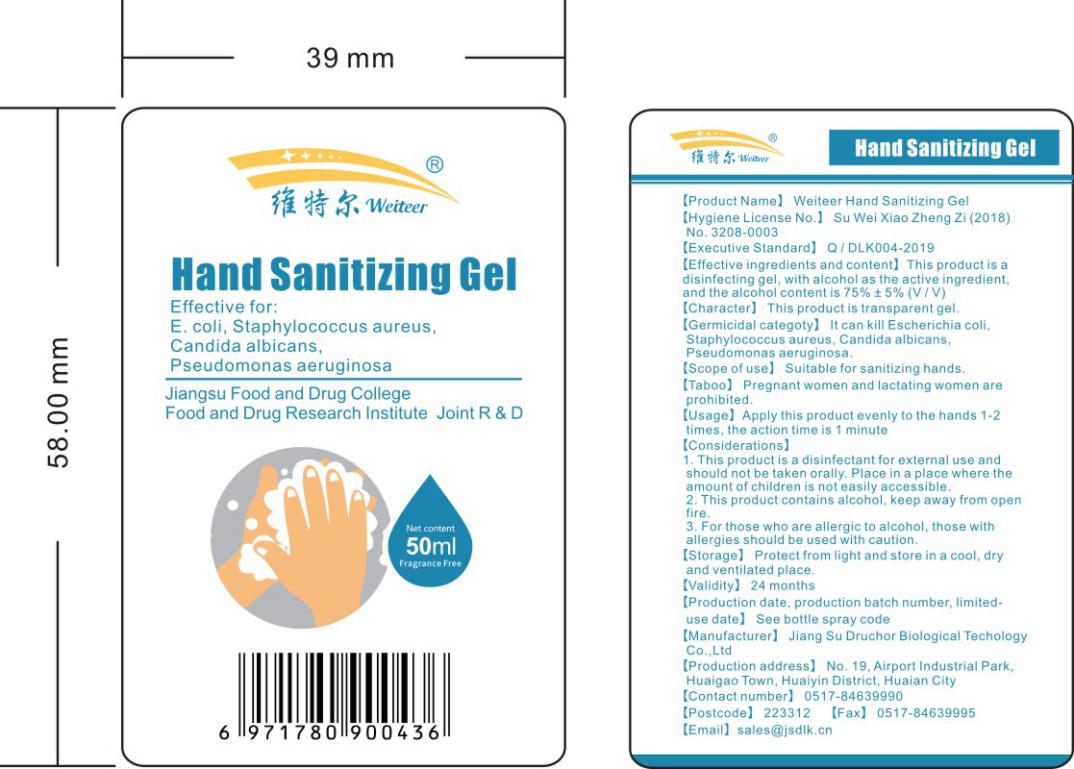 DRUG LABEL: Weiteer Hand Sanitizing Gel
NDC: 55868-002 | Form: GEL
Manufacturer: Jiangsu Druchor Biological Technology Co., Ltd.
Category: otc | Type: HUMAN OTC DRUG LABEL
Date: 20200608

ACTIVE INGREDIENTS: ALCOHOL 37.5 mL/50 mL
INACTIVE INGREDIENTS: WATER; SORBITOL; PHENOXYETHANOL; TROLAMINE; METHYL BENZOATE; PROPYLENE GLYCOL; GLYCERIN; CARBOMER HOMOPOLYMER, UNSPECIFIED TYPE

DOSAGE AND ADMINISTRATION

Protect from light and store in a cool, dry and ventilated place.

INACTIVE INGREDIENT

Water,Glycerin,CarbomerU20,Triethanolamine,PhenoXyaethanolum,Sorbitol,essence,1,2-Propanediol

INDICATIONS AND USAGE

Apply this product evenly to the hands 1-2 times, the action time is 1 minute

ACTIVE INGREDIENT

Ethyl Alcohol

keep out of reach of children

PURPOSE

Disinfection
Sterilization

WARNINGS

1. This product is a disinfectant for external use and should not be taken orally. Place in a place where the amount of children is not easily accessible.
2. This product contains alcohol, keep away from open fire.
3. For those who are allergic to alcohol, those with allergies should be used with caution.